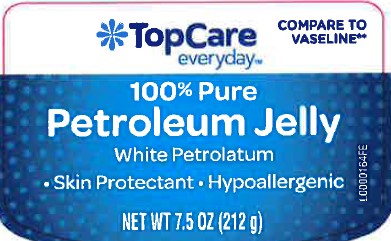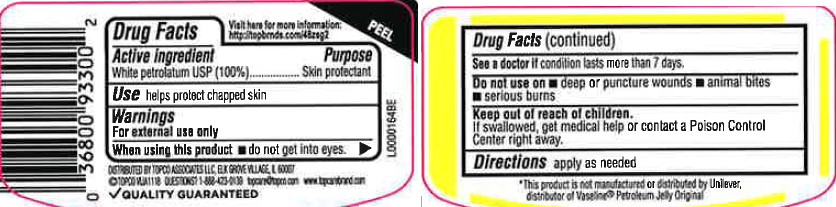 DRUG LABEL: Pure petroleum
NDC: 36800-069 | Form: JELLY
Manufacturer: Topco Associates LLC
Category: otc | Type: HUMAN OTC DRUG LABEL
Date: 20260213

ACTIVE INGREDIENTS: PETROLATUM 1 g/1 g

Top Care 069.001/069AA
Petroleum Jelly

Active ingredients

White Petrolatum USP (100%)

Purpose

Skin protectant

Uses

helps protect chapped skin

Warnings

For external use only

When using this product

- do not get into eyes

See a doctor if

condition lasts more than 7 days.

Do not use on

- deep or puncture wounds
- animal bites
- serious burns

Keep out of reach of children.

If swallowed, get medical help or contact a Poison Control Center right away.

Directions

apply as needed

Inactive Ingredients

None

Dislcaimer

*This product is not manufactured or distributed by Unliever, distributor of Vaseline®Petroleum Jelly Original

Adverse Reactions

DISTRIBUTED BY

TOPCO ASSOCIATES LLC

ELK GROVE VILLAGE, IL 60007

QUESTIONS? 1-888-423-0139

topcare@topco.com www.topcobrand.com

QUALITY GUARANTEED

Principal display panel

Compare to Vaseline®*

TopCare

everyday™

100% Pure

Petroleum Jelly

White Petrolatum

Skin Protectant - Hypoallergenic

NET WT 7.5 OZ (212 g)